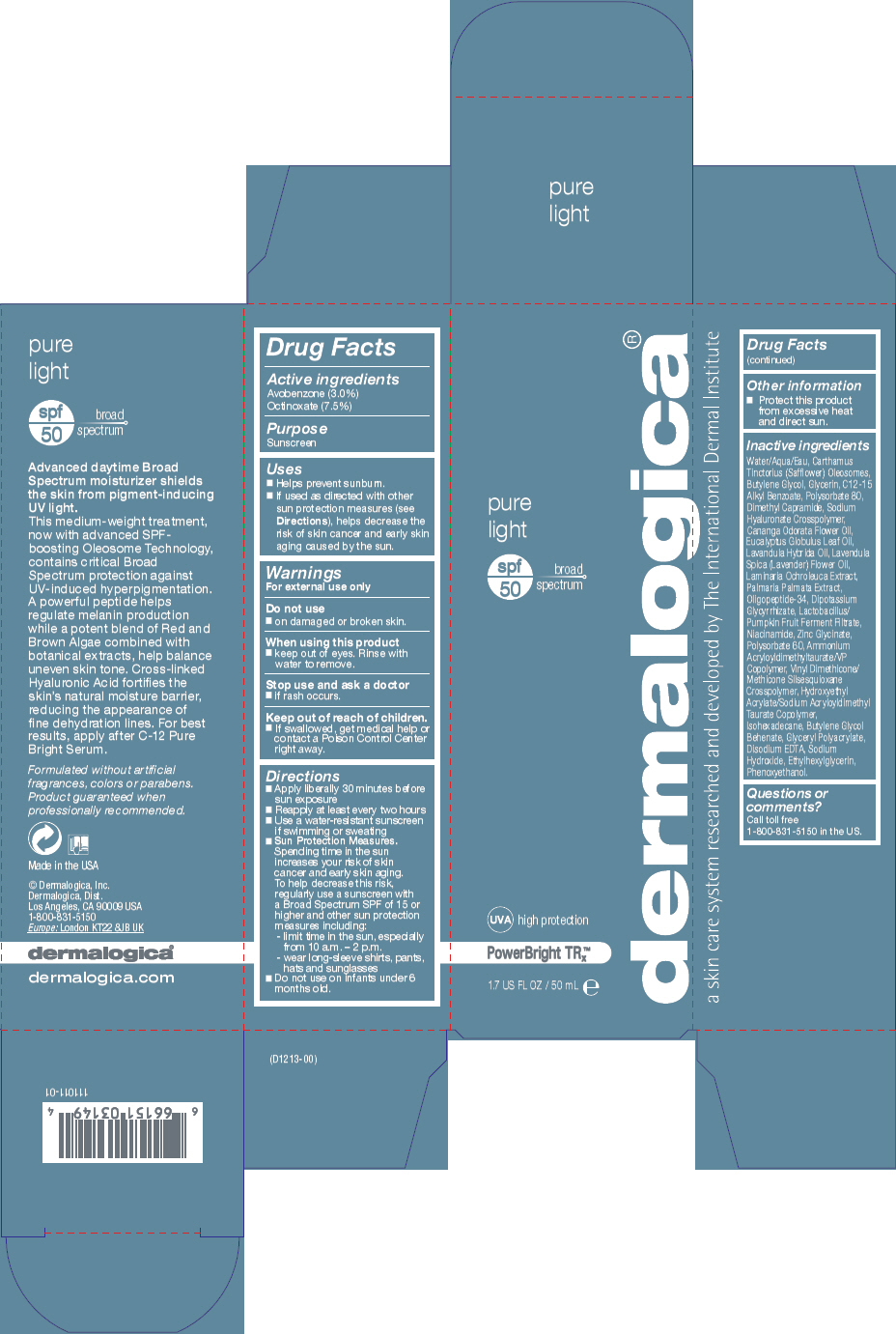 DRUG LABEL: PureLight 
NDC: 68479-213 | Form: LOTION
Manufacturer: Dermalogica, Inc.
Category: otc | Type: HUMAN OTC DRUG LABEL
Date: 20171211

ACTIVE INGREDIENTS: Avobenzone 30 mg/1 mL; Octinoxate 75 mg/1 mL
INACTIVE INGREDIENTS: Water; Carthamus Tinctorius Seed Oleosomes; Butylene Glycol; Glycerin; Alkyl (C12-15) Benzoate; Polysorbate 80; Dimethyl Capramide; Cananga Oil; Eucalyptus Oil; Lavandin Oil; Lavender Oil; Laminaria Ochroleuca; Dulse; Glycyrrhizinate Dipotassium; Niacinamide; Zinc Glycinate; Polysorbate 60; Ammonium Acryloyldimethyltaurate/VP Copolymer; Hydroxyethyl Acrylate/Sodium Acryloyldimethyl Taurate Copolymer (100000 MPA.S at 1.5%); Isohexadecane; Butylene Glycol Behenate; Edetate Disodium; Sodium Hydroxide; Ethylhexylglycerin; Phenoxyethanol

PureLight
SPF50

Drug Facts

Active ingredients

Avobenzone (3.0%)

Octinoxate (7.5%)

Purpose

Sunscreen

Uses

- Helps prevent sunburn.
- If used as directed with other sun protection measures (see Directions), helps decrease the risk of skin cancer and early skin aging caused by the sun.

Warnings

For external use only

Do not use

- on damaged or broken skin.

When using this product

- keep out of eyes. Rinse with water to remove.

Stop use and ask a doctor

- if rash occurs.

Keep out of reach of children.

- If swallowed, get medical help or contact a Poison Control Center right away.

Directions

- Apply liberally 30 minutes before sun exposure
- Reapply at least every two hours
- Use a water-resistant sunscreen if swimming or sweating
- Sun Protection Measures. Spending time in the sun increases your risk of skin cancer and early skin aging. To help decrease this risk, regularly use a sunscreen with a Broad Spectrum SPF of 15 or higher and other sun protection measures including:
  - limit time in the sun, especially from 10 a.m. – 2 p.m.
  - wear long-sleeve shirts, pants, hats and sunglasses
- Do not use on infants under 6 months old.

Other information

- Protect this product from excessive heat and direct sun.

Inactive ingredients

Water/Aqua/Eau, Carthamus Tinctorius (Safflower) Oleosomes, Butylene Glycol, Glycerin, C12-15 Alkyl Benzoate, Polysorbate 80, Dimethyl Capramide, Sodium Hyaluronate Crosspolymer, Cananga Odorata Flower Oil, Eucalyptus Globulus Leaf Oil, Lavandula Hybrida Oil, Lavendula Spica (Lavender) Flower Oil, Laminaria Ochroleuca Extract, Palmaria Palmata Extract, Oligopeptide-34, Dipotassium Glycyrrhizate, Lactobacillus/Pumpkin Fruit Ferment Filtrate, Niacinamide, Zinc Glycinate, Polysorbate 60, Ammonium Acryloyldimethyltaurate/VP Copolymer, Vinyl Dimethicone/Methicone Silsesquioxane Crosspolymer, Hydroxyethyl Acrylate/Sodium Acryloyldimethyl Taurate Copolymer, Isohexadecane, Butylene Glycol Behenate, Glyceryl Polyacrylate, Disodium EDTA, Sodium Hydroxide, Ethylhexylglycerin, Phenoxyethanol.

Questions or comments?

Call toll free 1-800-831-5150 in the US.

PRINCIPAL DISPLAY PANEL - 50 mL Tube Carton

pure
light

spf
50
broad
spectrum

UVA high protection

PowerBright TRx™

1.7 US FL OZ / 50 mL e

dermalogica®